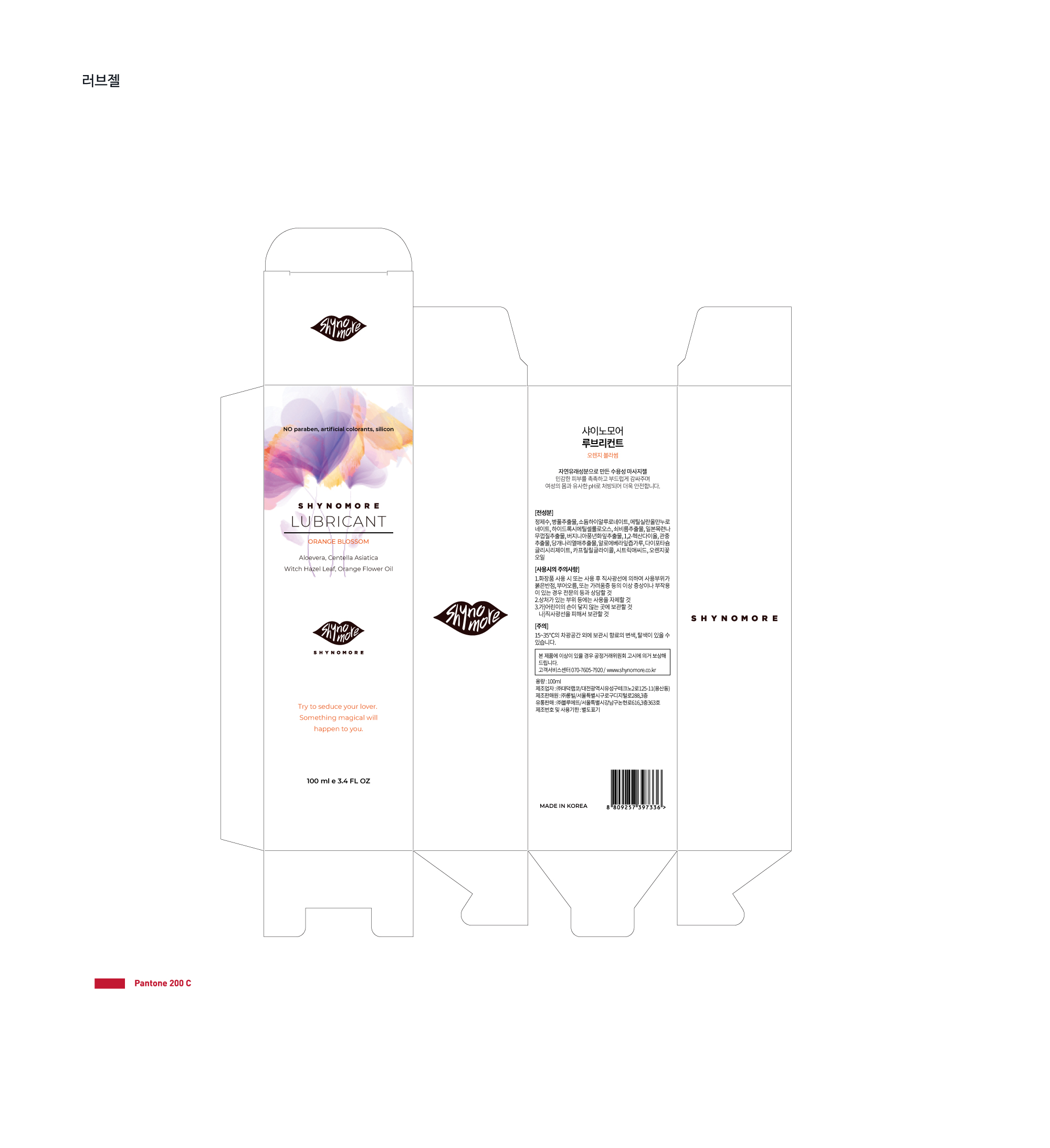 DRUG LABEL: SHYNOMORE LUBRICANT
NDC: 72072-0001 | Form: GEL
Manufacturer: Bluette Co., Ltd.
Category: otc | Type: HUMAN OTC DRUG LABEL
Date: 20180201

ACTIVE INGREDIENTS: CENTELLA ASIATICA 15 g/100 mL
INACTIVE INGREDIENTS: ALOE VERA LEAF; HAMAMELIS VIRGINIANA LEAF

ACTIVE INGREDIENT

Centella Asiatica Extract

INACTIVE INGREDIENT

Sodium Hyaluronate, Hamamelis Virginiana (Witch Hazel) Leaf Extract, etc.

PURPOSE

Water-soluble massage gel

keep out or reach of the children

INDICATIONS AND USAGE

With clean hands, dispense an appropriate amount and apply on skin, massaging gently

WARNINGS

Precautions for Use

If any of the following conditions occur, discontinue use immediately and consult a dermatologist. Continuous use will cause symptoms to worsen.

1) In case of skin reaction such as red spots, swelling, itch or irritation etc. during use

2) In case of the above skin reaction when applied area is exposed to direct sunlight

Do not use on damaged skin area such as wound, rash or skin infection

Storage and Handling

1) Close lid tightly after use

2) Keep out of reach of infants and children

3) Store in a cool, dry place away from direct sunlight

4) Avoid eye area

DOSAGE AND ADMINISTRATION

for external use only